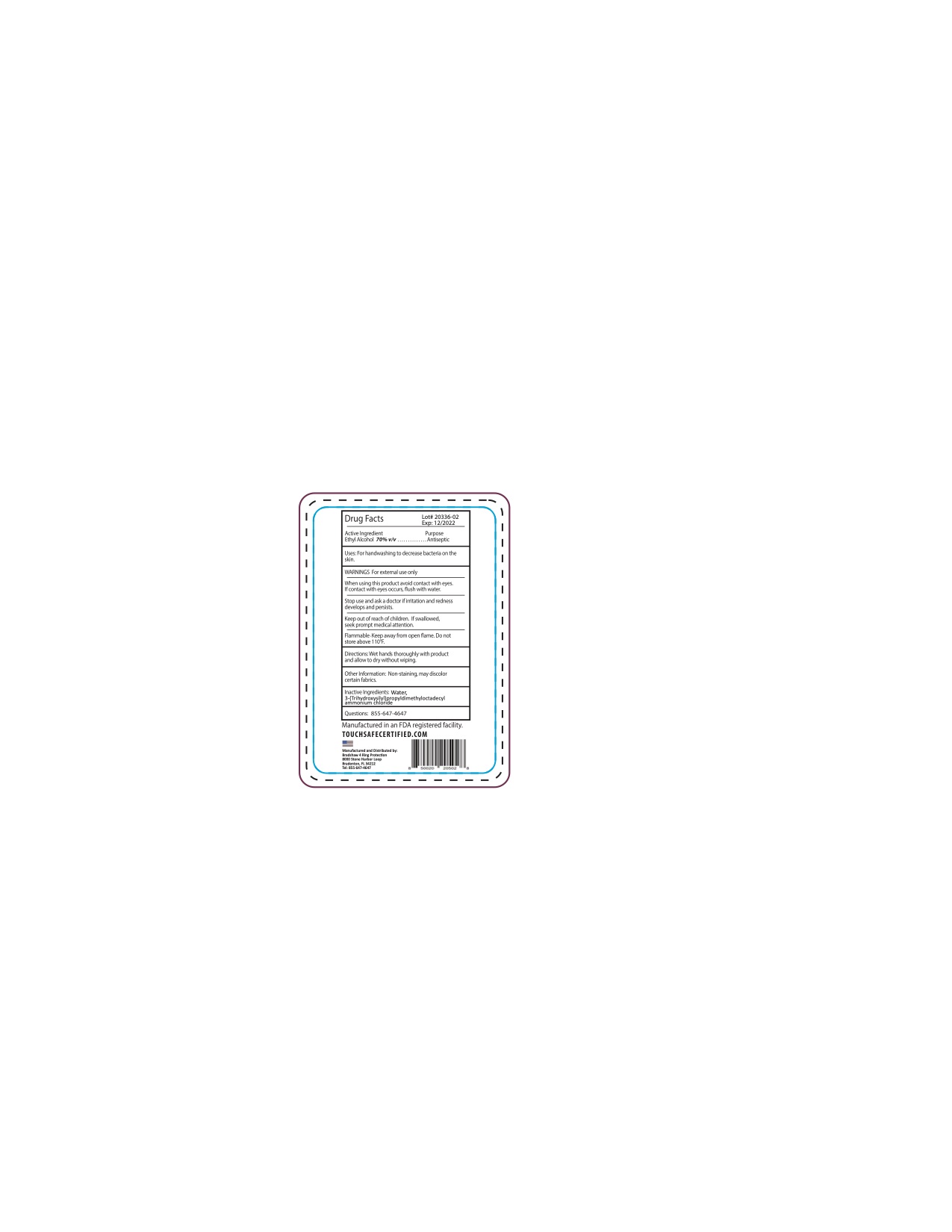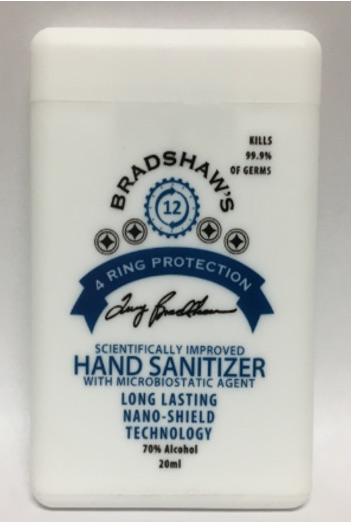 DRUG LABEL: Alcohol Agent Sanitizer
NDC: 58418-159 | Form: SPRAY
Manufacturer: Tropical Enterprises International, Inc.
Category: otc | Type: HUMAN OTC DRUG LABEL
Date: 20201231

ACTIVE INGREDIENTS: ALCOHOL 20.4 mL/30 mL
INACTIVE INGREDIENTS: WATER; OCTADECYLDIMETHYL(3-TRIHYDROXYSILYLPROPYL)AMMONIUM CHLORIDE

Formula # SC-077 70% Ethyl Alcohol Hand Sanitizer Spray with Spar additive.

Active Ingredient: Ethyl Alcohol 70% v/v

Stop use and ask a doctor if irritation and redness develops and persists.

Keep out of reach of children. If swallowed, seek prompt medical attention.

PURPOSE

Uses: For handwashing to decrease bacteria on the skin.

Questions: 855-647-4647

DOSAGE AND ADMINISTRATION

Directions: Wet hands thoroughly with product and allow to dry without wiping.

INACTIVE INGREDIENT

Inactive Ingredients: Water, 3-(Trihydroxysilyl)propyldimethyloctadecyl ammonium chloride

WARNINGS For external use only

SAFE HANDLING WARNING

Flammable. Keep away from open flame. Do not store above 110F.

Other information: Non-staining, may discolor certain fabrics.

INDICATIONS AND USAGE

Uses: For handwashing to decrease bacteria on the skin.

When using this product avoid contact with eyes. If contact with eyes occurs, flush with water.